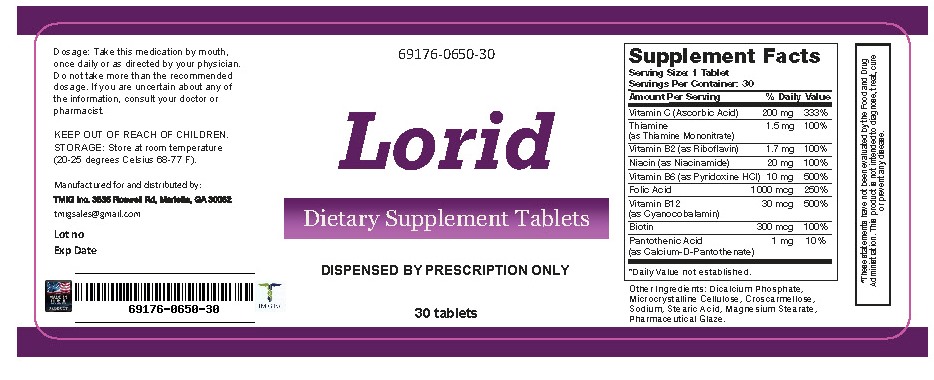 DRUG LABEL: Lorid
NDC: 69176-650 | Form: TABLET
Manufacturer: TMIG Inc.
Category: other | Type: DIETARY SUPPLEMENT
Date: 20180911

ACTIVE INGREDIENTS: ASCORBIC ACID 200 mg/1 1; FOLIC ACID 1 mg/1 1; METHYLCOBALAMIN .03 mg/1 1; RIBOFLAVIN 1.7 mg/1 1; NIACINAMIDE 20 mg/1 1; BIOTIN .3 mg/1 1; PANTOTHENIC ACID 1 mg/1 1; PYRIDOXINE HYDROCHLORIDE 8 mg/1 1; THIAMINE 1.5 mg/1 1
INACTIVE INGREDIENTS: MICROCRYSTALLINE CELLULOSE; CROSCARMELLOSE SODIUM; SHELLAC; STARCH, CORN; CALCIUM STEARATE; SILICON DIOXIDE

HEALTH CLAIM:

Lorid Tablets Dietary Supplement

Dispensed by Prescription†

Suppliment Facts
Serving Size: 1 tablet
Servings per container: 30

Amount per serving: % Daily Value

Vitamin C (as ascorbic acid) 200 mg 335%
Folic Acid 1mg 250%
Thiamine (as thiamine cononitrate) 1.5 mg 100%
Riboflavin 1.7 mg 100%
Niacin (as niacinamide) 20 mg 100%
Biotin 300 mcg 100%
Pantothenic Acid (as d-calcium pantothenate) 1mg 250%
Vitamin B6 (as pyridoxne HCL) 8 mg 400%
Vitamin B12 (as methylcobalamin) 30 mcg 500%

OTHER INGREDIENTS: microcrystalline cellulose, croscarmellose sodium, pharmacutical glaze, mono and diglycerides, starch, calcium stearate,silicon dioxide

DESCRIPTION:

Lorid Tablets is an orally administered prescription vitamin formulation for the clinical dietary management of suboptimal nutritional status in patients where advanced folate supplementation is required and nutritional supplementation in physiologically stressful conditions for maintenance of good health is needed.

WARNING AND PRECAUTIONS

This product is contraindicated in patients with a known hypersensitivity to any of the ingredients.

Lorid tablets should only be used under the direction and supervision of a licensed medical practitioner. Use with caution in patients that may have a medical condition, are pregnant, lactating, trying to conceive, under the age of 18, or taking medications.

Pregnancy and Lactation
Lorid is not intended for use in pregnant or lactating patients.

DOSAGE & ADMINISTRATION

Usual adult dose is 1 tablet once or twice daily or as prescribed by a licensed medical practitioner. Do not exceed daily recomended dosage without consulting your physician

HOW SUPPLIED HEALTH CLAIM:

Lorida tablets are supplied as tan, oblong shaped tablets in a child-resistant bottle of 30ct. (69176-0650-30*)

Dispensed by Prescription†

*TMIG Inc. does not represent these product codes to be National Drug Codes (NDC). Product codes are formatted according to standard industry practice, to meet the formatting requirement by pedigree reporting and supply-chain control including pharmacies.

† This product is a prescription-folate with or without other dietary ingredients that – due to increased folate levels increased risk associated with masking of B12 deficiency (pernicious anemia) requires administration under the care of a licensed medical practitioner (61 FR 8760).^1-3 The most appropriate way to ensure pedigree reporting consistent with these regulatory guidelines and safety monitoring is to dispense this product only by prescription (Rx). This is not an Orange Book product. This product may be administered only under a physician’s supervision and all prescriptions using this product shall be pursuant to state statutes as applicable. The ingredients, indication or claims of this product are not to be construed to be drug claims.

1. Federal Register Notice of August 2, 1973 (38 FR 20750)
2. Federal Register Notice of October 17, 1980 (45 FR 69043, 69044)
3. Federal Register Notice of March 5, 1996 (61 FR 8760)

STORAGE AND HANDLING:

Store at 20°-25°C (68°-77°F); excursions permitted to 15°-30°C (59°-86°F) [See USP Controlled Room Temperature.]

Protect from heat, light and moisture.

KEEP OUT OF THE REACH OF CHILDREN.

Tamper Evident: Do not use if seal is broken or missing.